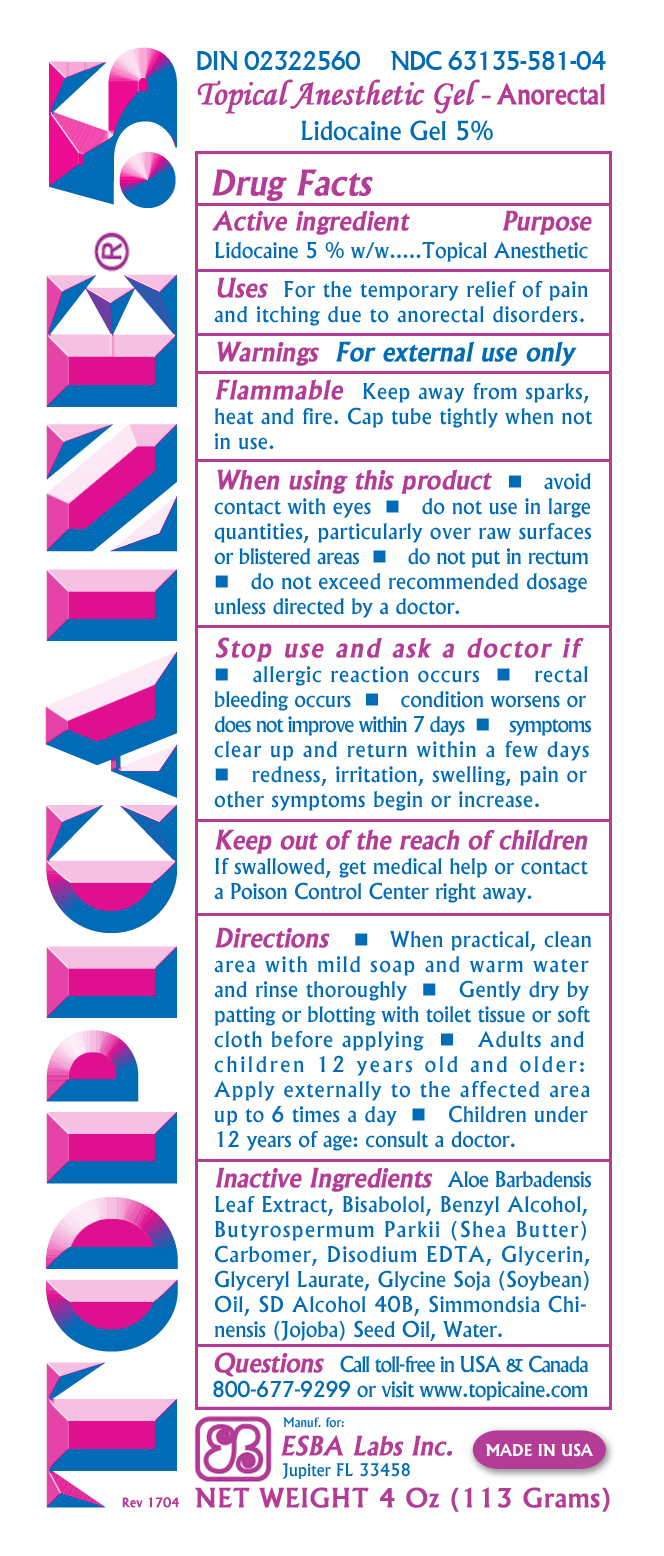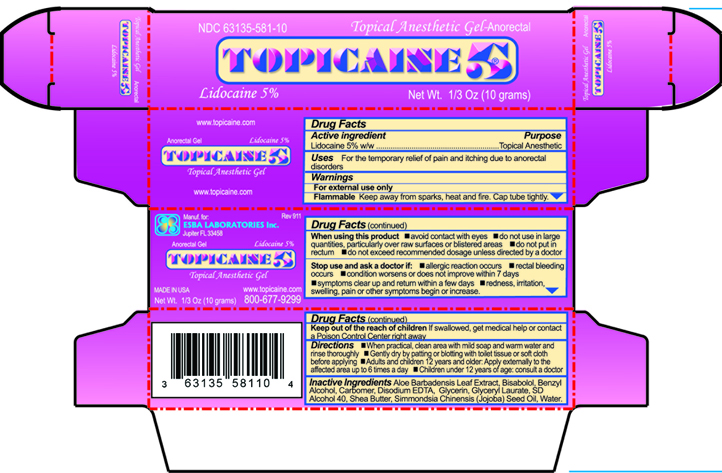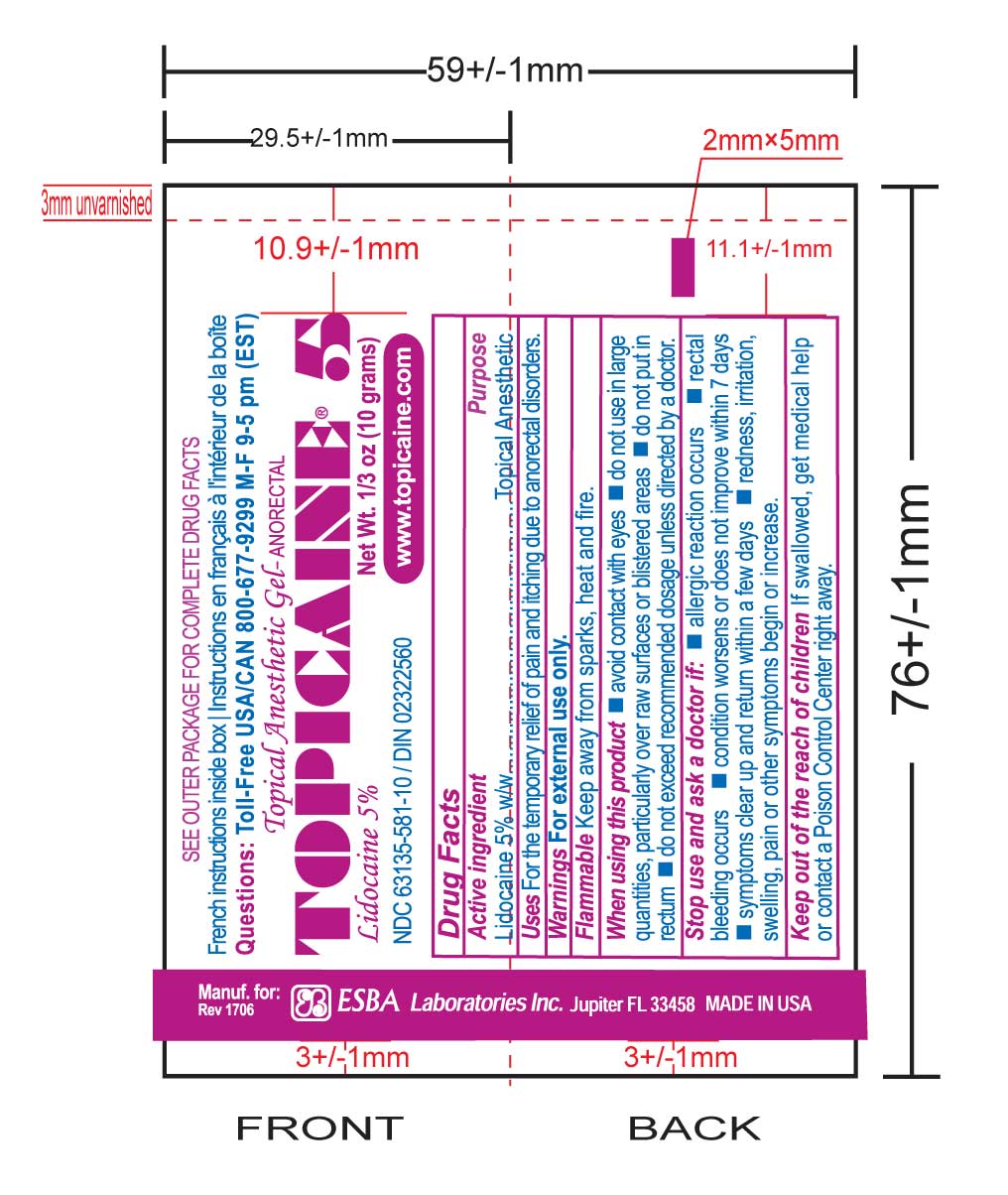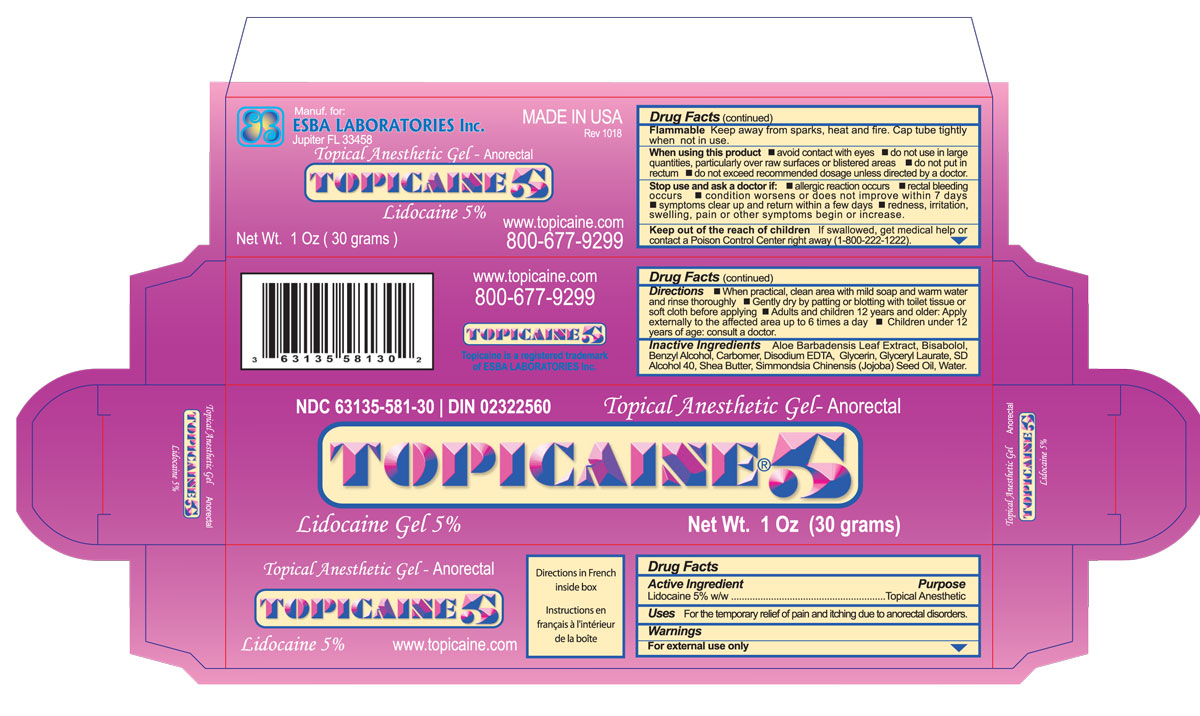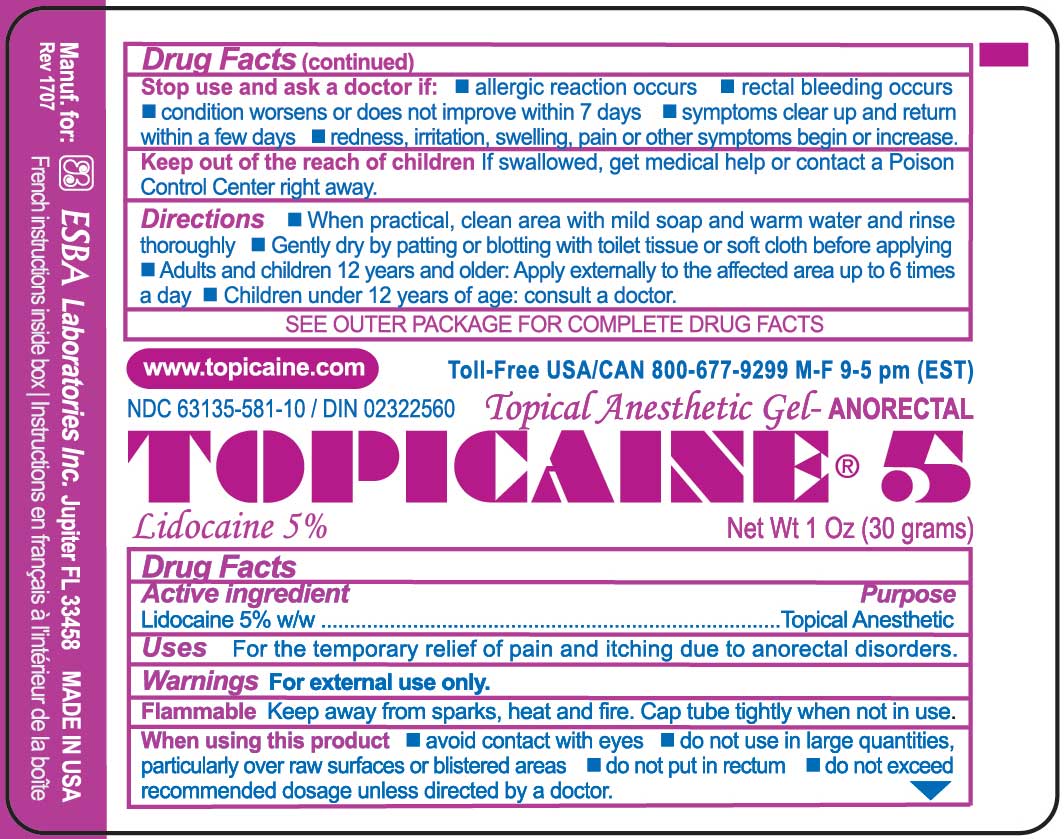 DRUG LABEL: TOPICAINE 5
NDC: 63135-581 | Form: GEL
Manufacturer: ESBA LABORATORIES INC.
Category: otc | Type: HUMAN OTC DRUG LABEL
Date: 20240919

ACTIVE INGREDIENTS: LIDOCAINE 5 g/100 g
INACTIVE INGREDIENTS: GLYCERIN 5 g/100 g; ALOE VERA LEAF 2 g/100 g; BENZYL ALCOHOL 0.8 g/100 g; .ALPHA.-BISABOLOL, (+/-)- 1 g/100 g; SHEA BUTTER 2.5 g/100 g; EDETATE DISODIUM 0.025 g/100 g; POLYACRYLIC ACID (8000 MW) 0.6 g/100 g; GLYCERYL LAURATE 2.5 g/100 g; ALCOHOL 36.75 g/100 g

TOPICAINE 5

Active Ingredient

Lidocaine 5% w/w

Purpose

Topical Anesthetic

Uses

For the temporary relief of pain and itching due to anorectal disorders.

Warnings

For external use only

Flammable Keep away from sparks, heat and fire. Cap tube tightly when not in use.

When using this product

- avoid contact with eyes
- do not use in large quantities, particularly over raw surfaces or blistered areas
- do not put in rectum
- do not exceed recommended dosage unless directed by a doctor

Stop use and ask a doctor if:

- allergic reaction occurs
- rectal bleeding occurs
- condition worsens or does not improve within 7 days
- symptoms clear up and return within a few days
- redness, irritation, swelling, pain or other symptoms begin or increase.

Keep out of the reach of children

If swallowed, get medical help or contact a Poison Control Center right away.

Inactive Ingredients

Aloe Barbadensis Leaf Extract, Bisabolol, Benzyl Alcohol, Carbomer, Disodium EDTA, Glycerin, Glyceryl Laurate, SD Alcohol 40, Shea Butter, Simmondsia Chinensis (Jojoba) Seed Oil, Water.

Directions

- When practical, clean area with mild soap and warm water and rinse thoroughly
- Gently dry by patting or blotting with toilet tissue or soft cloth before applying
- Adults and children 12 years old and older: Apply externally to the affected area up to 6 times a day
- Children under 12 years of age: consult a doctor.

Label on tube and outer carton

Labeling printed on tube of Topicaine 5% 10 g

Outer carton of Topicaine 5% 10 g tube

Label affixed to tube of Topicaine 5 % 30 g tube

Outer carton of Topicaine 5 % 30 g tube:

Label affixed to tube to Topicaine 5% 113 g